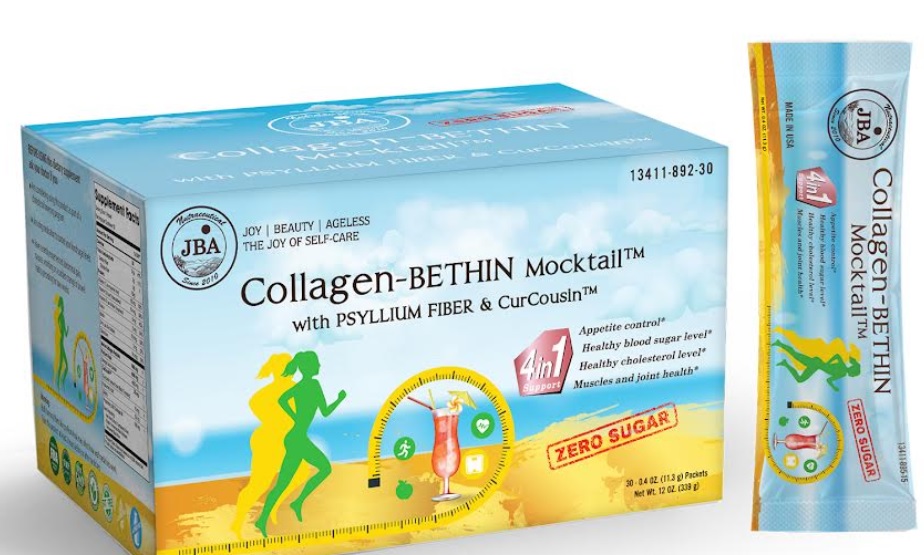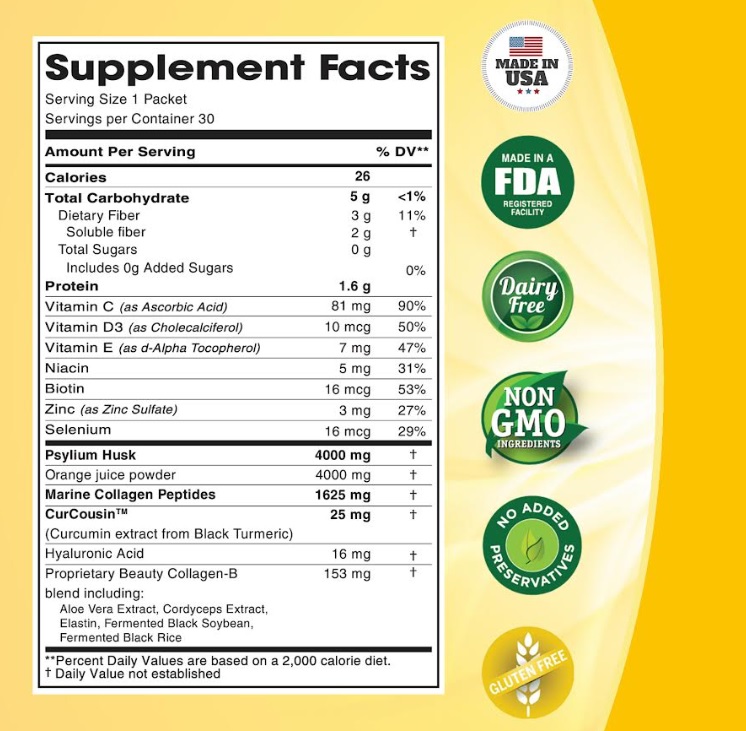 DRUG LABEL: JBA Collagen-BETHIN Mocktail with PSYLLIUM FIBER CurCousin
NDC: 13411-892 | Form: POWDER
Manufacturer: Advanced Pharmaceutical Services, Inc. Dba Affordable Quality Pharmaceuticals
Category: other | Type: DIETARY SUPPLEMENT
Date: 20230130

ACTIVE INGREDIENTS: ASCORBIC ACID 81 mg/11.3 g; CHOLECALCIFEROL 10 ug/11.3 g; .ALPHA.-TOCOPHEROL 7 mg/11.3 g; NIACINAMIDE 5 mg/11.3 g; BIOTIN 16 ug/11.3 g; ZINC SULFATE MONOHYDRATE 3 mg/11.3 g; SELENIUM 16 ug/11.3 g; MARINE COLLAGEN, SOLUBLE 1625 mg/11.3 g; PSYLLIUM HUSK 4000 mg/11.3 g; ORANGE JUICE 4000 mg/11.3 g; CURCUMIN 25 mg/11.3 g; HYALURONIC ACID 16 mg/11.3 g; ALOE VERA LEAF 38 mg/11.3 g; OPHIOCORDYCEPS SINENSIS 38 mg/11.3 g; ELASTIN BOVINE 4 mg/11.3 g; SOYBEAN 38 mg/11.3 g; RICE BRAN 38 mg/11.3 g
INACTIVE INGREDIENTS: ANHYDROUS CITRIC ACID; FD&C RED NO. 40; KOLLICOAT SR 30D; MANNITOL; DIMETHICONE; SUCRALOSE; SUCROSE; STEVIA REBAUDIUNA LEAF

Identity

Dietary supplement

Warnings

BEFORE USING this dietary supplement ask your doctor if you

- Are considering using this product as part of a cholesterol lowering program
- Are using medication to control your blood sugar levels
- Have recently experienced abdominal pain, nausea, vomiting or a sudden change in bowel habits persisting for two weeks.

Warning:
Bulk forming fibers like psyllium husk may affect how well medicines work. Take this product at least 2 hours before or after medicines.

Direction

For adult 12 years and older

1. Pour 1 packet in empty glass
2. Mix briskly with 8 oz or more of cool liquid
3. Drink promptly and enjoy!

Appetite controls* & Healthy blood sugar levels* Take 1 packet before each meal up to 3 times per day

Heart Health* & Digestive Health* Take 1 packet 2 times per day

Safe handling warning

JBA® Collagen-BETHIN Mocktail™ with PSYLLIUM FIBER & CurCousin™

Supper charge your weight Management* & Reverse the signs of Aging and Boost Your Immune System*
PSYLLIUM FIBER HELPS SUPPORT:

- Appetite Control*
- Digestive Health *
- Healthy Blood Sugar Level*
- Heart Health by Lowering cholesterol level*

JBA COLLAGEN-B HELPS SUPPORT:

- Strengthen hair, skin and nails*
- Muscles and joint health*
- Control blood sugar*
- Immune Health*

HEALTH CLAIM

CurCousin™

- Branded ingredient from Black Turmeric
- 65 patents – 13 publications – 1 clinical study
- Help manage the healthy body weight by inhibiting adipogenesis (fat cells)

Diet low in saturated fat and cholesterol that include 7 grams of soluble fiber per day from psyllium husk, as in Collagen-Bethin, may reduce the risk of heart disease by lowering cholesterol. One serving of Collagen-Bethin has 3.4 grams of this soluble fiber.

* These statements have not been evaluated by the Food & Drug Administration. This product is not intended to diagnose, treat, cure, or prevent any disease.